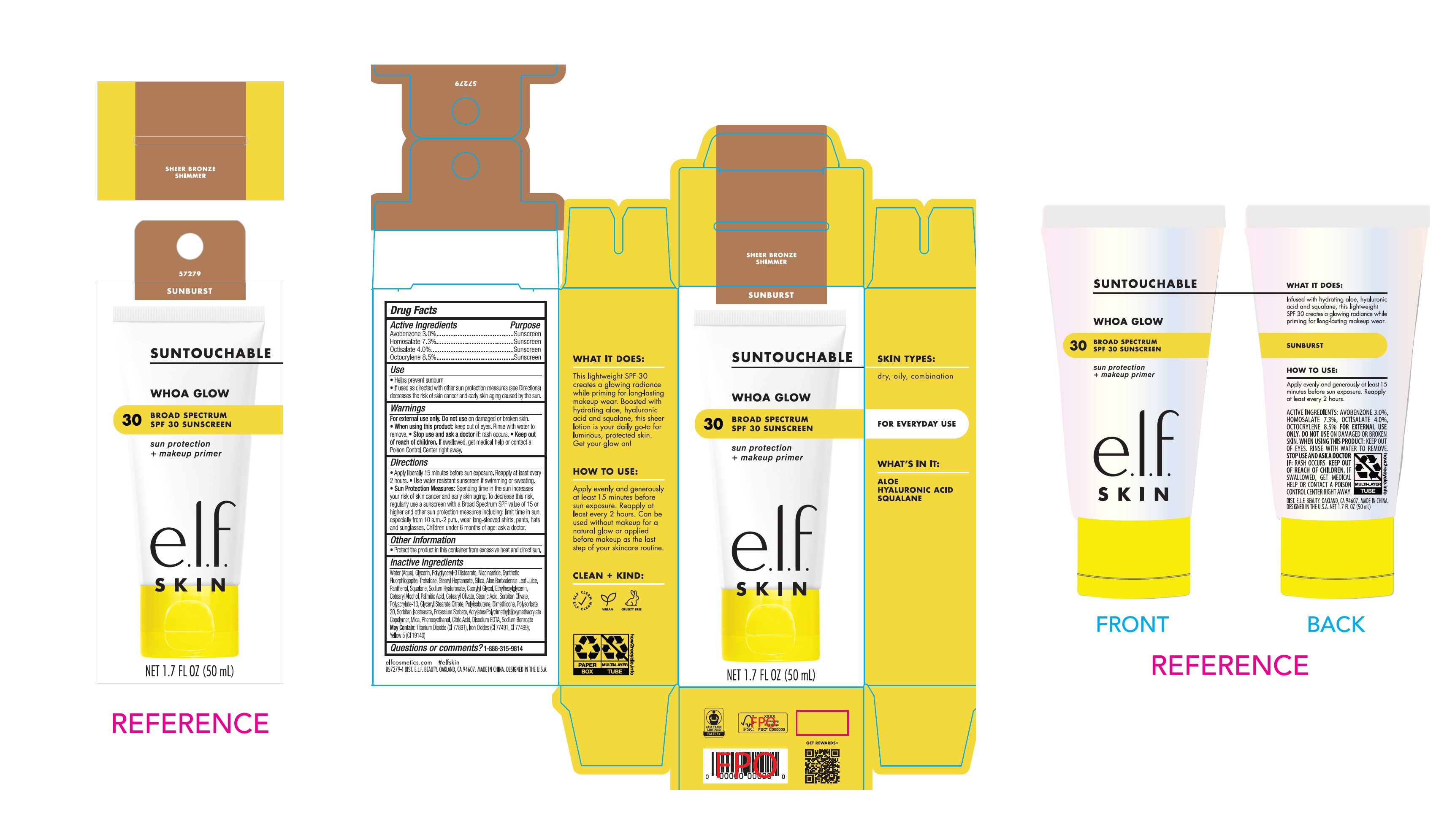 DRUG LABEL: e l f Whoa Glow Broad Spectrum SPF 30 Sunscreen Sheer Bronze Shimmer Sunburst
NDC: 76354-451 | Form: CREAM
Manufacturer: e.l.f. Cosmetics, Inc
Category: otc | Type: HUMAN OTC DRUG LABEL
Date: 20251107

ACTIVE INGREDIENTS: AVOBENZONE 30 mg/1 mL; HOMOSALATE 73 mg/1 mL; OCTISALATE 40 mg/1 mL; OCTOCRYLENE 85 mg/1 mL
INACTIVE INGREDIENTS: WATER; GLYCERIN; POLYGLYCERYL-3 DISTEARATE; NIACINAMIDE; MAGNESIUM POTASSIUM ALUMINOSILICATE FLUORIDE; TREHALOSE; STEARYL HEPTANOATE; SILICON DIOXIDE; ALOE VERA LEAF; PANTHENOL; SQUALANE; HYALURONATE SODIUM; CAPRYLYL GLYCOL; ETHYLHEXYLGLYCERIN; CETOSTEARYL ALCOHOL; PALMITIC ACID; CETEARYL OLIVATE; STEARIC ACID; SORBITAN OLIVATE; POLYACRYLATE-13; GLYCERYL STEARATE CITRATE; DIMETHICONE, UNSPECIFIED; POLYSORBATE 20; SORBITAN ISOSTEARATE; POTASSIUM SORBATE; MICA; PHENOXYETHANOL; CITRIC ACID MONOHYDRATE; EDETATE DISODIUM; SODIUM BENZOATE

e.l.f. Whoa Glow Broad Spectrum SPF 30 Sunscreen, Sheer Bronze Shimmer Sunburst

Active Ingredients

Avobenzone 3.0%

Homosalate 7.3%

Octisalate 4.0%

Octocrylene 8.5%

Purpose

Sunscreen

Use

- Helps prevent sunburn
- If used as directed with other sun protection measures (see Directions) decreases the risk of skin cancer and early skin aging caused by the sun.

Warnings

For external use only.

• Do not use

on damaged or broken skin.

• When using this product:

Keep out of eyes. Rinse with water to remove.

• Stop use and ask a doctor if:

rash occurs.

• Keep out of reach of children.

If swallowed, get medical help or contact a Poison Control Center right away.

Directions

- Apply liberally 15 minutes before sun exposure. Reapply at least every 2 hours.
- Use water resistant sunscreen if swimming or sweating.
- Sun Protection Measures: Spending time in the sun increases your risk of skin cancer and early skin aging. To decrease this risk, regularly use a sunscreen with a Broad Spectrum SPF value of 15 or higher and other sun protection measures including: limit time in sun, especially from 10 a.m.-2 p.m., wear long-sleeved shirts, pants, hats and sunglasses. Children under 6 months of age: ask a doctor

Other Information

- Protect the product in this container from excessive heat and direct sun.

Inactive Ingredients

Water (Aqua), Glycerin, Polyglyceryl-3 Distearate, Niacinamide, Synthetic Fluorphogopite, Trehalose, Stearyl Heptanoate, Silica, Aloe Barbadensis Leaf Juice, Panthenol, Squalane, Sodium Hyaluronate, Caprylyl Glycol, Ethylhexylglycerin, Cetearyl Alcohol, Palmitic Acid, Cetearyl Olivate, Stearic Acid, Sorbitan Olivate, Polyacrylate-13, Glyceryl Stearate Citrate, Polyisobutene, Dimethicone, Polysorbate 20, Sorbitan Isostearate, Potassium Sorbate, Acrylates/Polytrimethylsiloxymethacrylate Copolymer, Mica, Phenoxyethanol, Citric Acid, Disodium EDTA, Sodium Benzoate May Contain:Titanium Dioxide (CI 77891), Iron Oxides (CI 77491, CI 77499), Yellow 5 (CI 19140)

Questions or comments?

1-888-315-9814